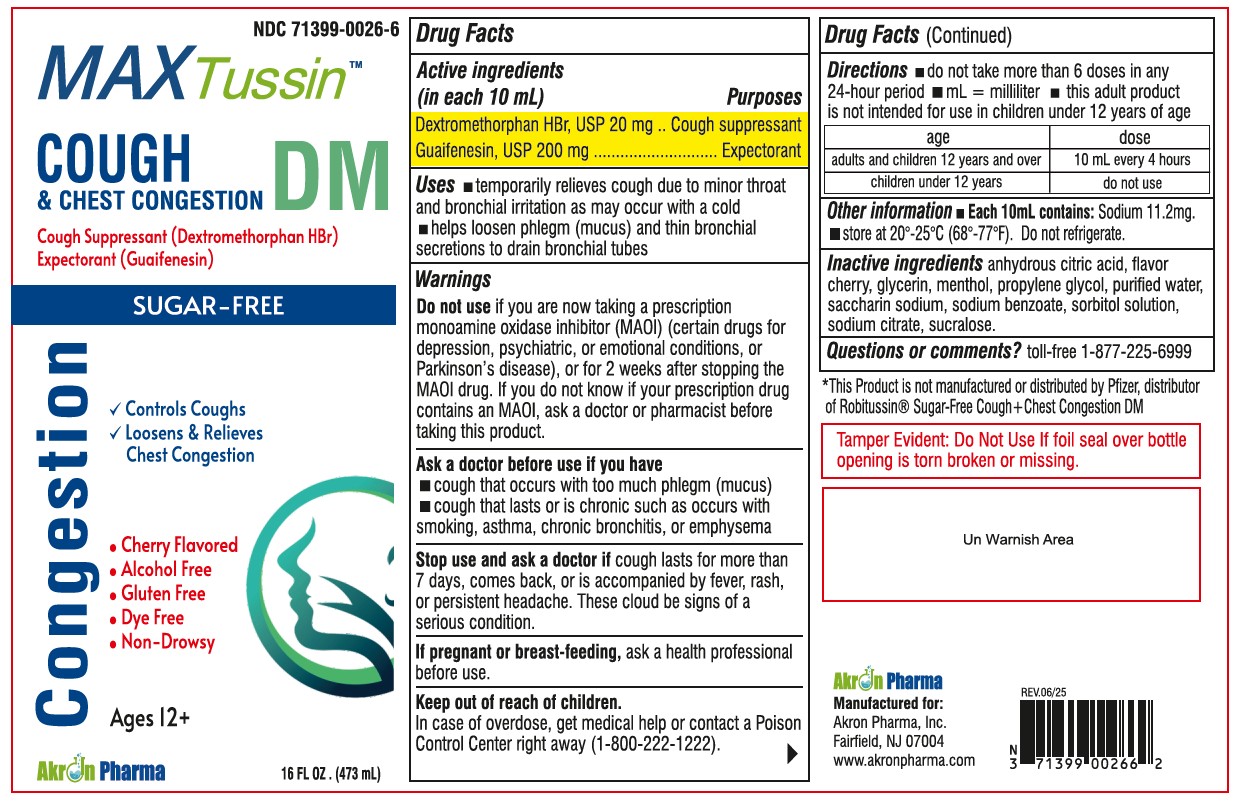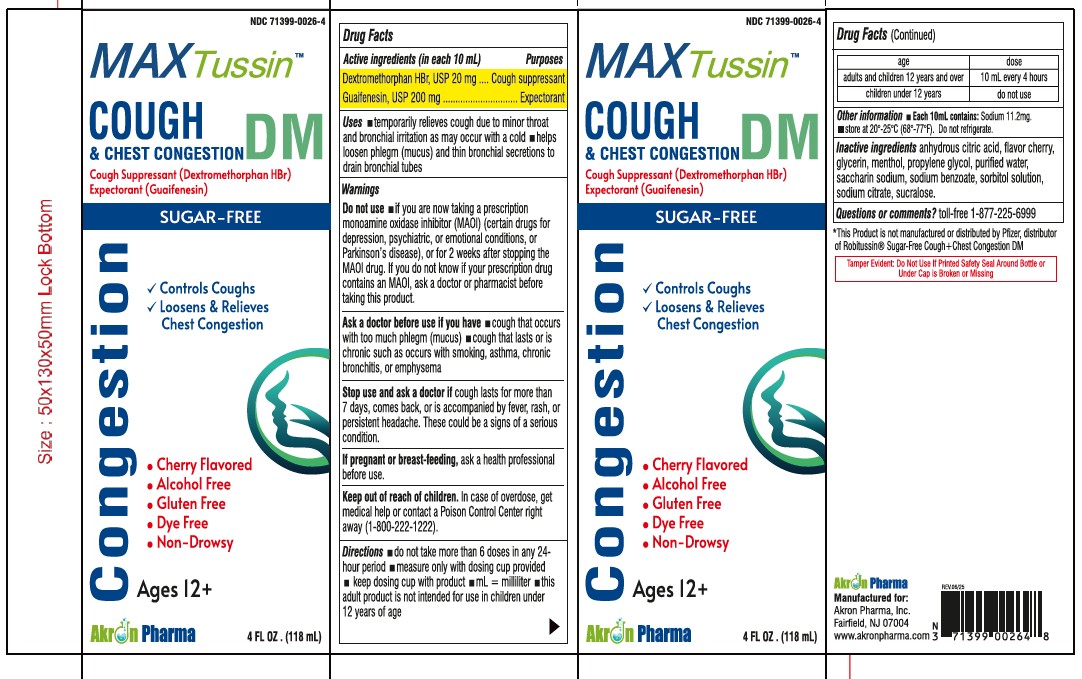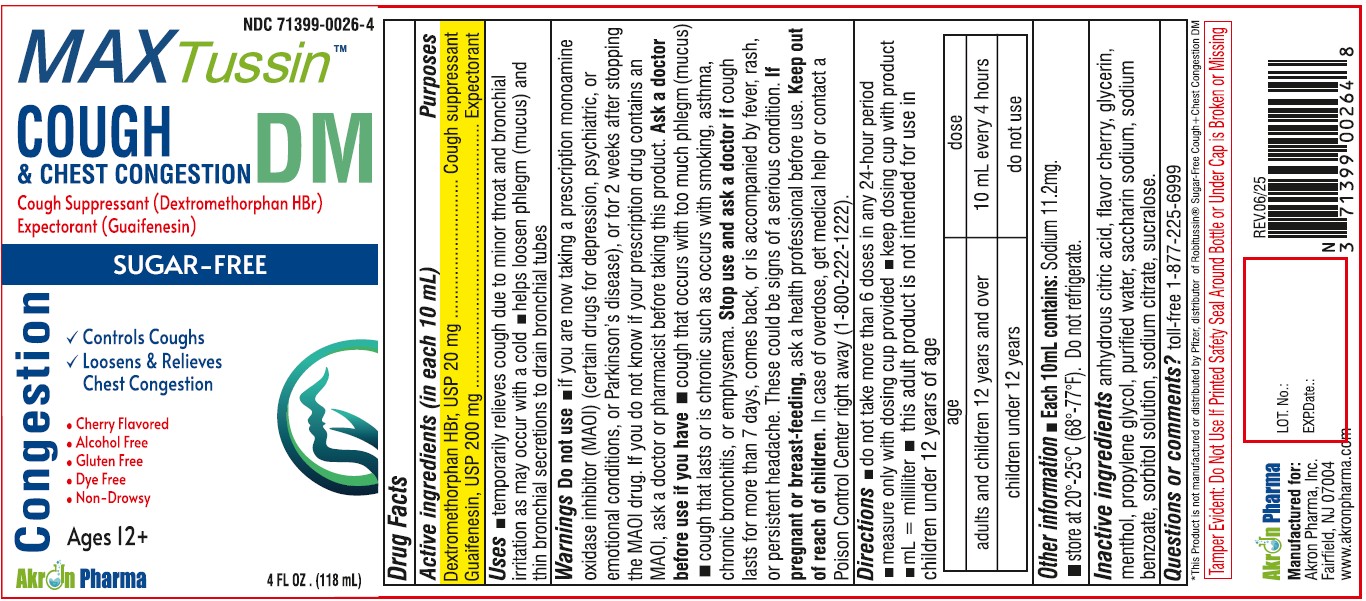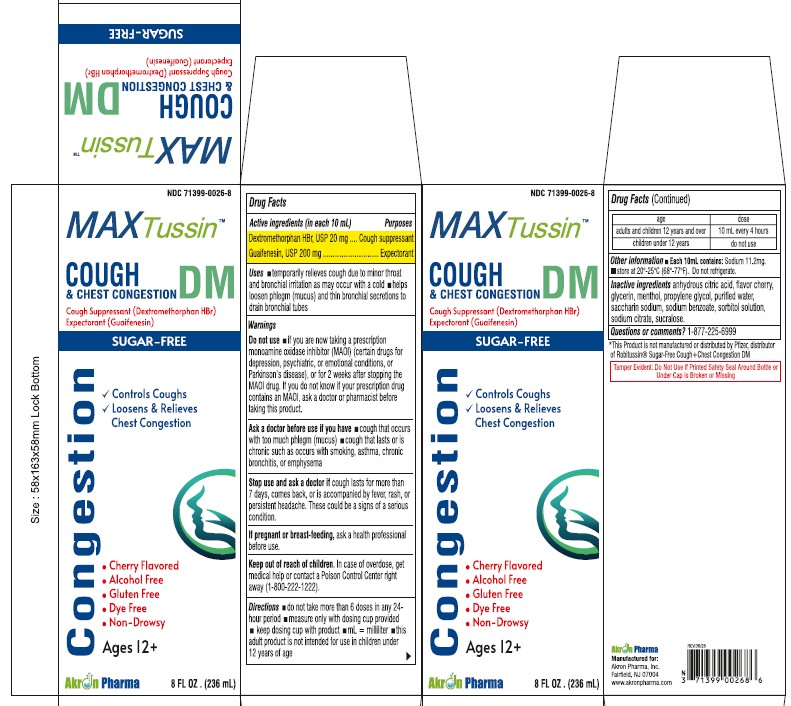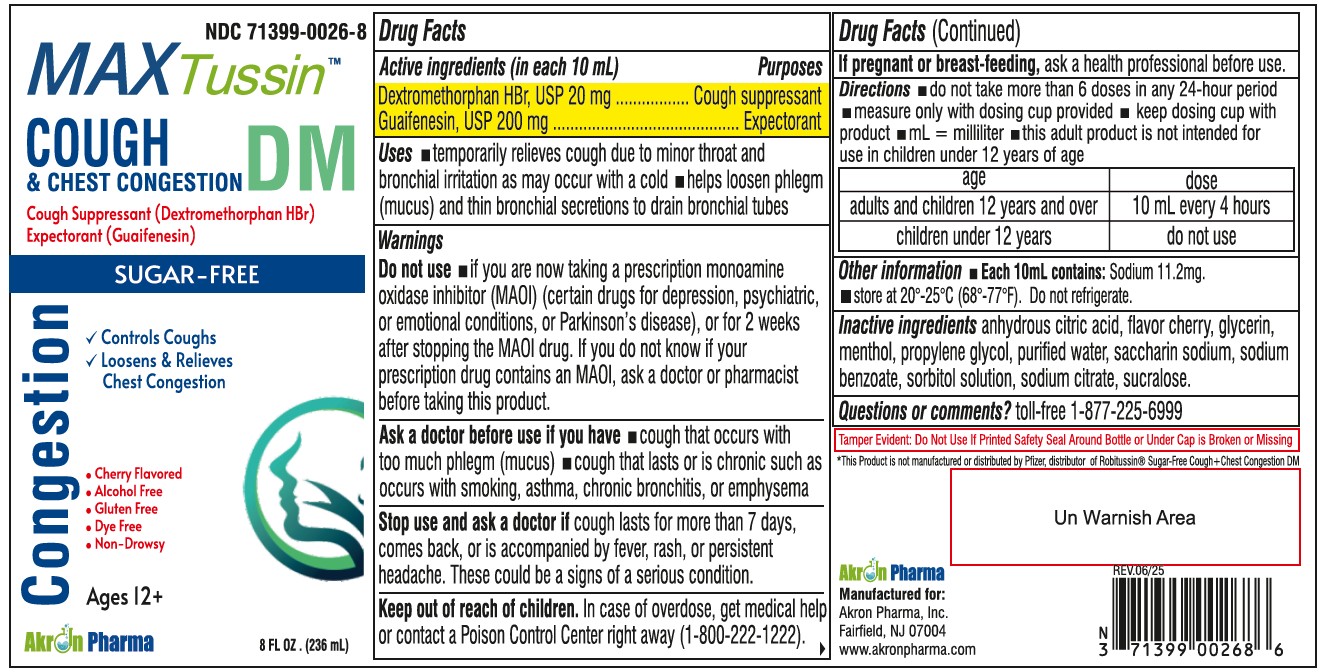 DRUG LABEL: MAX Tussin Cough and Chest Congestion DM Sugar Free
NDC: 71399-0026 | Form: LIQUID
Manufacturer: Akron Pharma Inc.
Category: otc | Type: HUMAN OTC DRUG LABEL
Date: 20251027

ACTIVE INGREDIENTS: DEXTROMETHORPHAN HYDROBROMIDE 20 mg/10 mL; GUAIFENESIN 200 mg/10 mL
INACTIVE INGREDIENTS: ANHYDROUS CITRIC ACID; GLYCERIN; MENTHOL; PROPYLENE GLYCOL; WATER; SACCHARIN SODIUM; SODIUM BENZOATE; SORBITOL SOLUTION; SODIUM CITRATE; SUCRALOSE

MAX Tussin Cough and Chest Congestion DM Sugar Free
Guaifenesin 200mg and Dextromethorphan Hbr 20mg per 10ml
Cherry Flavor
Alcohol-Free

Active ingredients (in each 10 mL)

Dextromethorphan HBr 20 mg

Guaifenesin 200 mg

Purposes

Cough suppressant

Expectorant

Uses

- temporarily relieves cough due to minor throat and bronchial irritation as may occur with a cold
- helps loosen phlegm (mucus) and thin bronchial secretions to drain bronchial tubes

Warnings

Do not use

if you are now taking a prescription monoamine oxidase inhibitor (MAOI) (certain drugs for depression, psychiatric or emotional conditions, or Parkinson’s disease), or for 2 weeks after stopping the MAOI drug. If you do not know if your prescription drug contains an MAOI, ask a doctor or pharmacist before taking this product.

Ask a doctor before use if you have

- cough that occurs with too much phlegm (mucus)
- cough that lasts or is chronic such as occurs with smoking, asthma, chronic bronchitis or emphysema

If pregnant or breast-feeding,

ask a health professional before use.

Stop use and ask a doctor if

cough lasts more than 7 days, comes back, or is accompanied by fever, rash, or persistent headache. These could be signs of a serious condition.

Keep out of reach of children.

In case of overdose, get medical help or contact a Poison Control Center right away (1-800-222-1222).

Directions

- do not take more than 6 doses in any 24-hour period
- measure only with dosing cup provided
- keep dosing cup with product
- mL= milliliter
- this adult product is not intended for use in children under 12 years of age

age | dose
adults and children 12 years and over | 10 mL every 4 hours
children under 12 years | do not use

Other information

- Phenylketonurics: contains Phenylalanine 30 mg per 10 mL
- store between 20-25ºC(68-77ºF). Do not refrigerate

Inactive ingredients

anhydrous citric acid, flavor cherry, glycerin, menthol, purified water, saccharin sodium, sodium benzoate, sorbitol solution, sodium citrate, sucralose.

Questions or comments?

toll-free 1-877-225-6999

Manufactured for:

Akron Pharma, Inc.

Fairfield, NJ 07004

www.akronpharma.com